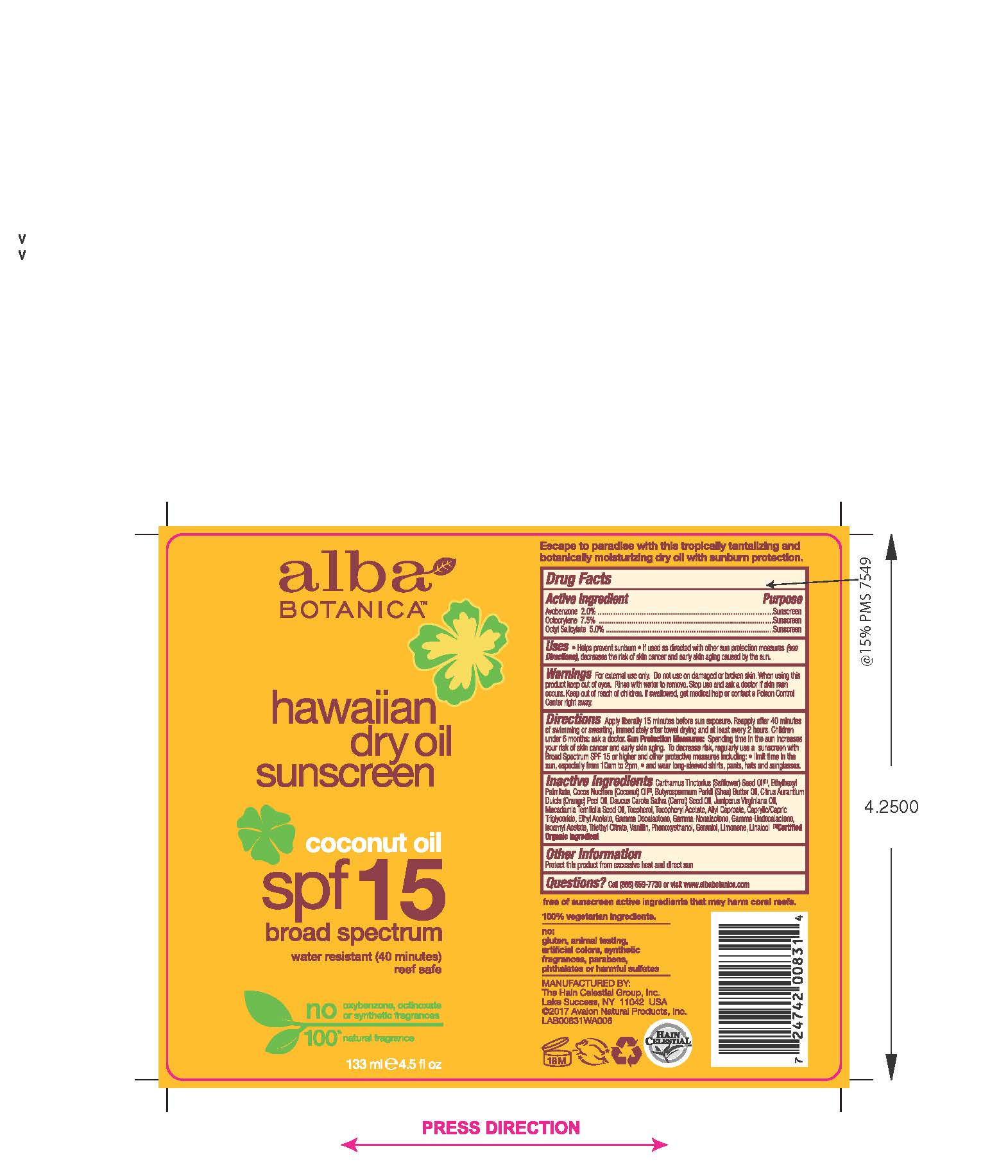 DRUG LABEL: AL0083103 Alba Hawaiian Dry Coconut Sunscreen SPF15
NDC: 61995-2083 | Form: OIL
Manufacturer: The Hain Celestial Group, Inc.
Category: otc | Type: HUMAN OTC DRUG LABEL
Date: 20210205

ACTIVE INGREDIENTS: OCTISALATE 5 g/133 g; OCTOCRYLENE 7.5 g/133 g; AVOBENZONE 2 g/133 g
INACTIVE INGREDIENTS: ETHYLHEXYL PALMITATE; SAFFLOWER OIL; COCONUT OIL; SHEA BUTTER; CARROT SEED OIL; MACADAMIA OIL; TOCOPHEROL; .ALPHA.-TOCOPHEROL ACETATE; PHENOXYETHANOL; ORANGE OIL; MEDIUM-CHAIN TRIGLYCERIDES; JUNIPERUS VIRGINIANA OIL

Alba Botanica Coconut Dry Oil Sunscreen SPF 15

WARNINGS AND PRECAUTIONS

For external use only. Do not use on damaged or broken skin. When using this product keep out of eyes. Rinse with water to remove. Stop use and ask a doctor if skin rash occurs.

ACTIVE INGREDIENT

Avobenzone - 2.0%

Octyl Salicylate - 5.0%

Octocrylene - 7.5%

Purpose: Sunscreen

Keep out of reach of children. If swallowed, get medical help or contact Poison Center right away.

INACTIVE INGREDIENT

Carthamus Tinctorius (Safflower) Seed Oil (1), Ethylhexyl Palmitate, Cocos Nucifera (Coconut) Oil (1), Butyrospermum Parkii (Shea) Butter, Citrus Aurantium Dulcis (Orange) Peel Oil, Daucus Carota Sativa (Carrot) Seed Oil, Juniperus Virginiana Oil, Macadamia Ternifolia Seed Oil, Tocopherol, Tocopheryl Acetate, Phenoxyethanol, Caprylic/Capric Trigluceride, Allyl Caproate, Ethyl Acetate.

(1) Certified Organic Ingredient

DOSAGE AND ADMINISTRATION

Apply liberally before Sun exposure. Reapply after 40 minutes of swimming or sweating, immediately aftertowel drying and at least every 2 hours.Children under 6 months: ask a doctor. Sun Protection Measures: Spending time in the sun increases your risk of skin cancerand early skin aging.To decrease risk, regulary use sunscreen with Broad Spectrum SPF 15 or higher and other protective measures including: limit time in the sun, especially from 10am to 2pm, and wear long-sleevedshirts, pants, hats and sunglases.